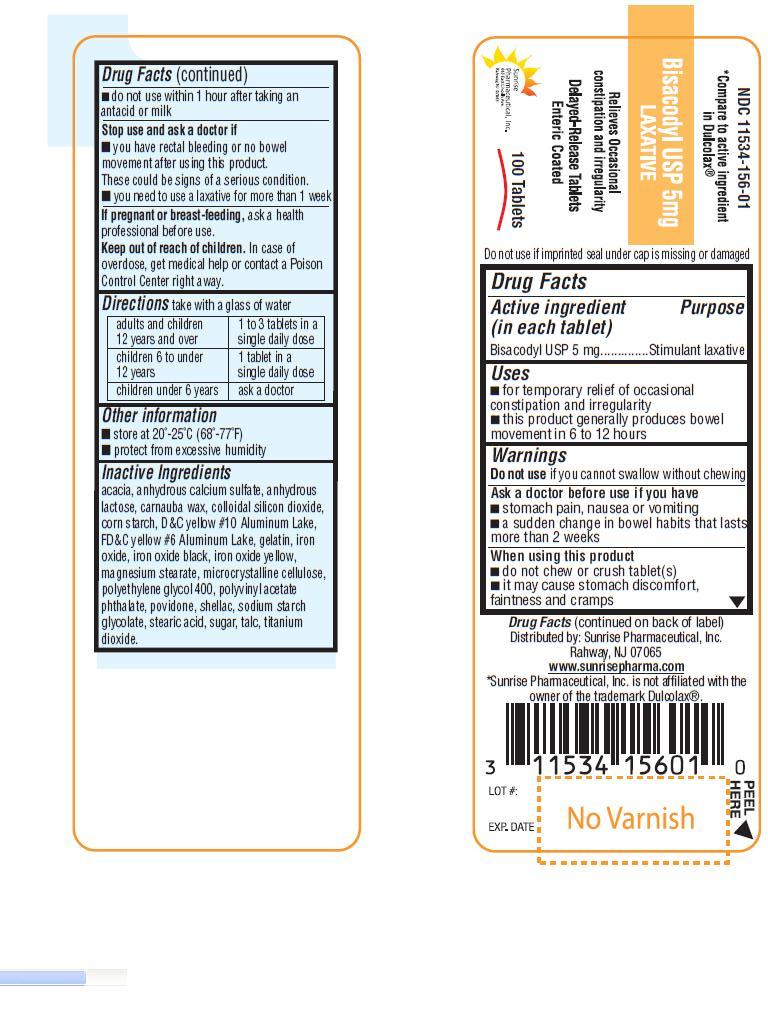 DRUG LABEL: Bisacodyl
NDC: 11534-156 | Form: TABLET, DELAYED RELEASE
Manufacturer: Sunrise Pharmaceutical Inc
Category: otc | Type: HUMAN OTC DRUG LABEL
Date: 20130729

ACTIVE INGREDIENTS: BISACODYL 5 mg/1 1
INACTIVE INGREDIENTS: ACACIA; CALCIUM SULFATE ANHYDROUS; ANHYDROUS LACTOSE; CARNAUBA WAX; SILICON DIOXIDE; STARCH, CORN; D&C YELLOW NO. 10; FD&C YELLOW NO. 6; GELATIN; FERROSOFERRIC OXIDE; FERRIC OXIDE YELLOW; MAGNESIUM STEARATE; CELLULOSE, MICROCRYSTALLINE; POLYETHYLENE GLYCOL 400; POVIDONE; SHELLAC; SODIUM STARCH GLYCOLATE TYPE A POTATO; STEARIC ACID; SUCROSE; TALC; TITANIUM DIOXIDE; POLYVINYL ACETATE PHTHALATE 

Bisacodyl USP 5 mg Laxative

OTC - ACTIVE INGREDIENT

Bisacodyl USP 5mg.

OTC - PURPOSE

Stimulant laxative.

INDICATIONS AND USAGE

For temporary relief of occasional constipation and irregularity

This product generally produces bowel movement in 6 to 12 hours.

WARNINGS

Do not use if you cannot swallow without chewing.

OTC - ASK DOCTOR

If you have

Stomach pain, nausea or vomiting

A sudden change in bowel habits that lasts for more than 2 weeks.

OTC - WHEN USING

Do not chew or crush tablet(s).

It may cause stomach discomfort, faintness and cramps.

Do not use within 1 hour after taking an antacid or milk.

OTC - STOP USE

And ask a doctor if:

You have rectal bleeding or no bowel movement after using this product. These could be signs of serious condition.

You need to use laxative for more than 1 week

OTC - PREGNANCY OR BREAST FEEDING

Ask a health professional before use.

OTC - KEEP OUT OF REACH OF CHILDREN

In case of overdose, get medical help or contact a Poison Control Center right away.

DOSAGE AND ADMINISTRATION

Take with a glass of water

Adults and children 12 years and over | 1 to 3 tablets in a single daily dose
Children 6 to under 12 years | 1 tablet in a single daily dose
Children under 6 years | Ask a doctor

OTHER INFORMATION

Store at 20(-25(C(68(-77(F). Protect from excessive humidity.

INACTIVE INGREDIENT

Acacia, anhydrous calcium sulfate, anhydrous lactose, carnauba wax, colloidal silicon dioxide, corn starch, D&C yellow #10 Aluminum Lake, FD&C yellow #6 Aluminum Lake, gelatin, iron oxide, iron oxide black, iron oxide yellow, magnesium stearate, microcrystalline cellulose, polyethylene glycol 400, polyvinyl acetate phthalate, povidone, shellac, sodium starch glycolate, stearic acid, sugar, talc, titanium dioxide.